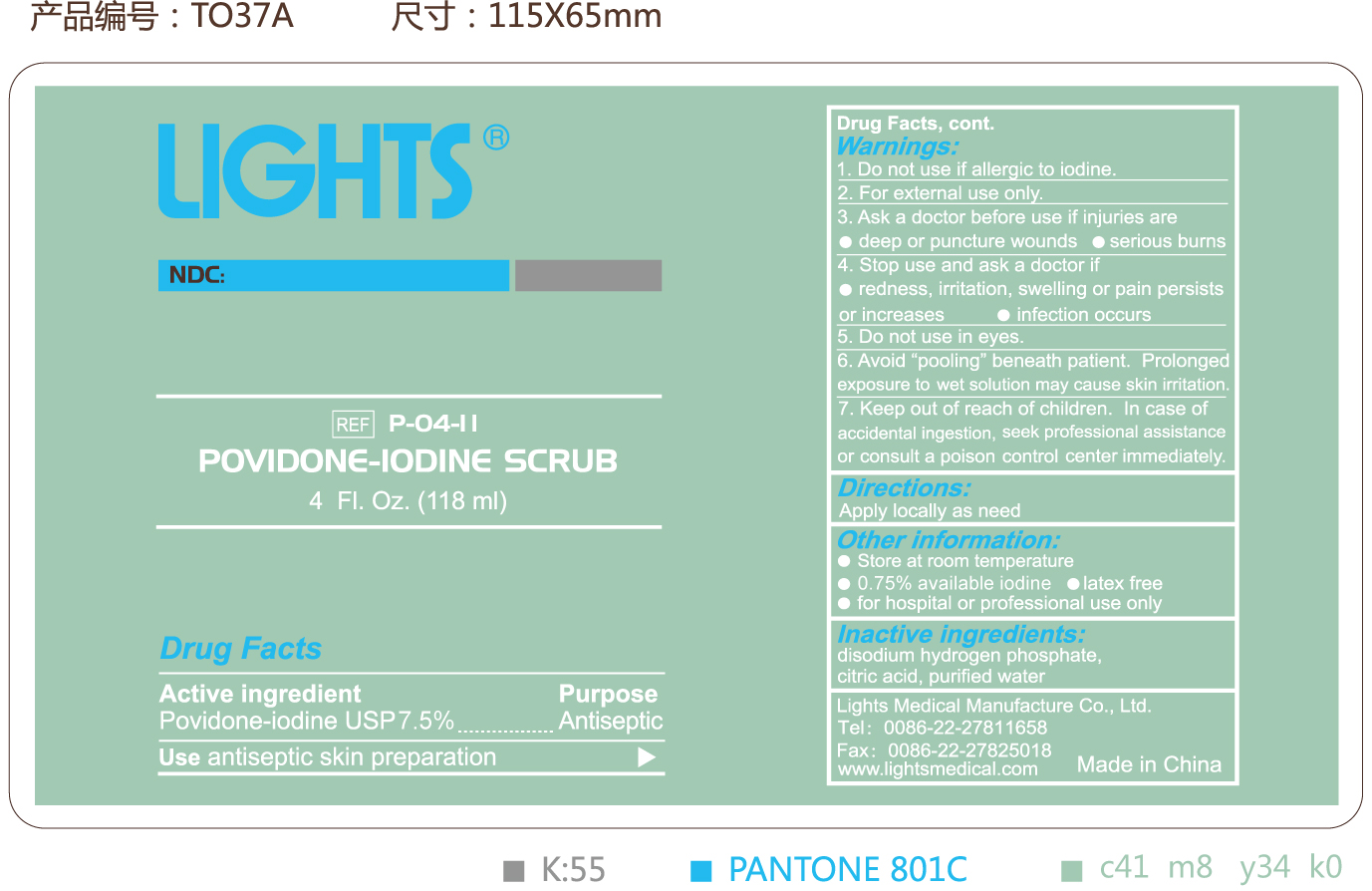 DRUG LABEL: Lights Povindone Iodine Scrub
NDC: 61333-205 | Form: SOLUTION
Manufacturer: Lights Medical Manufacture Co., Ltd.
Category: otc | Type: HUMAN OTC DRUG LABEL
Date: 20260121

ACTIVE INGREDIENTS: POVIDONE-IODINE 0.75 g/100 g
INACTIVE INGREDIENTS: CITRIC ACID MONOHYDRATE; WATER; SODIUM PHOSPHATE DIBASIC DIHYDRATE

61333-205

Active Ingredient: Povidone-Iodine USP (7.5%)

Purpose: Antiseptic

Use:

Antiseptic skin preparation

Warnings:

Do not use if allergic to iodine

For external use only

Do not use in eyes

Avoid pooling beneath patient. Prolonged exposure to wet solution may cause skiin irritation.

Ask a doctor before use if injuries are

deep or puncture wounds

Serious burns

Stop use and ask a doctor if

Redness, irritation, swelling or pain persisits or increases

Infection occurs

Keep out of reach of children. In case of a accidental ingestion,, seek professional assistance or consult a poison control center immediately

Directions:

Apply locally as needed.

Other information

- Store at room temperature
- 0.75% available iodine
- Latax free
- For hospital or professional use only

Inactive Ingredient

Citric acid, purified water, Disodium hydrogen phosphate